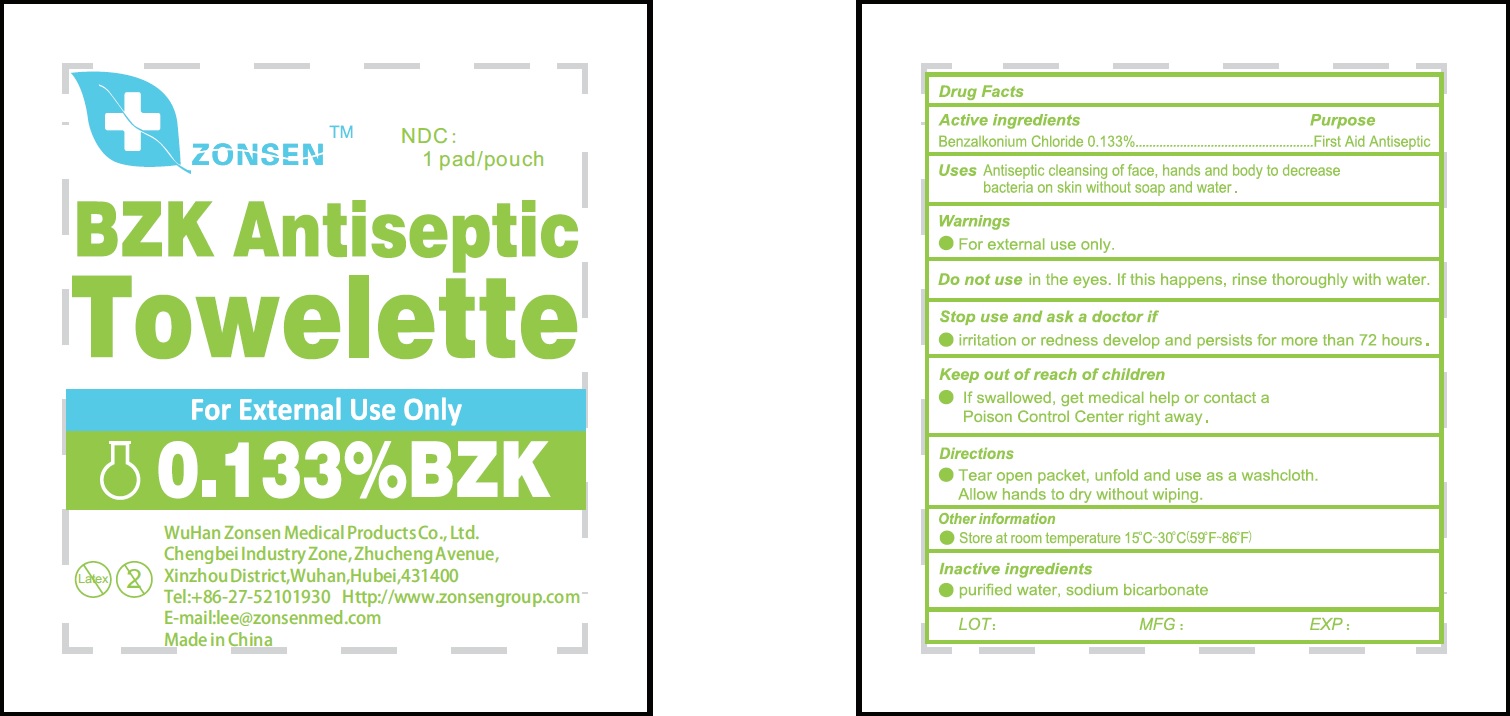 DRUG LABEL: Zonsen BZK Antiseptic
NDC: 72932-002 | Form: SWAB
Manufacturer: Wuhan Zonsen Medical Products Co., Ltd.
Category: otc | Type: HUMAN OTC DRUG LABEL
Date: 20190520

ACTIVE INGREDIENTS: BENZALKONIUM CHLORIDE 1.33 mg/1 mL
INACTIVE INGREDIENTS: WATER; SODIUM BICARBONATE

Zonsen BZK Antiseptic Towelette

Active Ingredients

Benzalkonium Chloride 0.133%

Purpose

First Aid Antiseptic

Use

Antiseptic cleansing of face, hands and body to decrease bacteria on skin without soap and water.

Warnings

- For external use only.

Do not use

in the eyes. If this happens, rinse thoroughly with water.

Stop use and ask a doctor

if irritation and redness develop and persists for more than 72 hours.

Keep out of reach of children.

If swallowed, get medical help or contact a Poison Control Center right away.

Directions

- Tear open packet, unfold and use as a washcloth. Allow hands to dry without wiping.

Other information

Store at room temperature 15°C-30°C(59°F-86°F)

Inactive Ingredients:

purified water, sodium bicarbonate